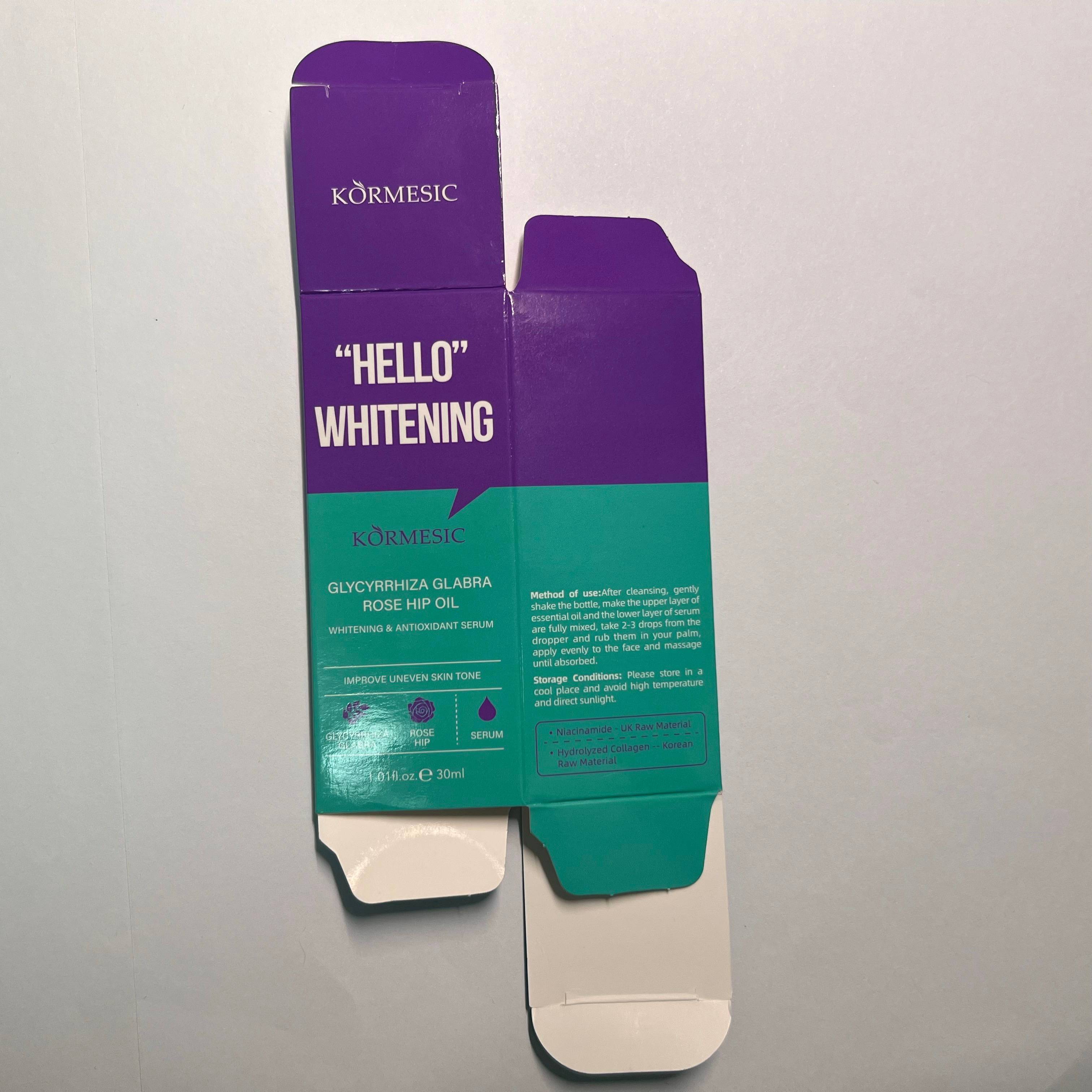 DRUG LABEL: kormesic glycyrrhiza glabra  rose hip oil whitening antioxidant serum
NDC: 84372-052 | Form: LOTION
Manufacturer: Shenzhen Zhumeng Times Technology Co., Ltd.
Category: otc | Type: HUMAN OTC DRUG LABEL
Date: 20240910

ACTIVE INGREDIENTS: HYALURONIC ACID 5 g/30 mL
INACTIVE INGREDIENTS: GLYCERIN; PHENOXYETHANOL; SORBITOL; WATER; MINERAL OIL

Active ingredients

Hyaluronic Acid 5%

Purpose

to regrow hair on the top of the scalp

Uses

Provides comprehensive skin care benefits including brightening, antioxidant, moisturizing, anti-aging and soothing repair. The combination of these ingredients can help improve skin tone and increase skin hydration

Warnings

Keep out of reach of children. Do not swallow.

Dosage and administration

For external use only.

Do not use

Due to different skin types, if you experience sensitivity or discomfort after use, please discontinue use.

When using section

After cleansing, gently shake the bottle to mix the top layer of essential oils with the bottom layer of essence. Take 2-3 drops from the dropper, rub in the palm of your hand, apply evenly to the face and massage until absorbed.

stop use

Due to different skin types, if you experience sensitivity or discomfort after use, please discontinue uses

Keep out of reach of children.lf swallowed, get medical help or contacta Poison Control Center right away.

Inactive ingredients

Water,Paraffinum Liquidum,Glycerin,Sorbitol,Phenoxyethanol